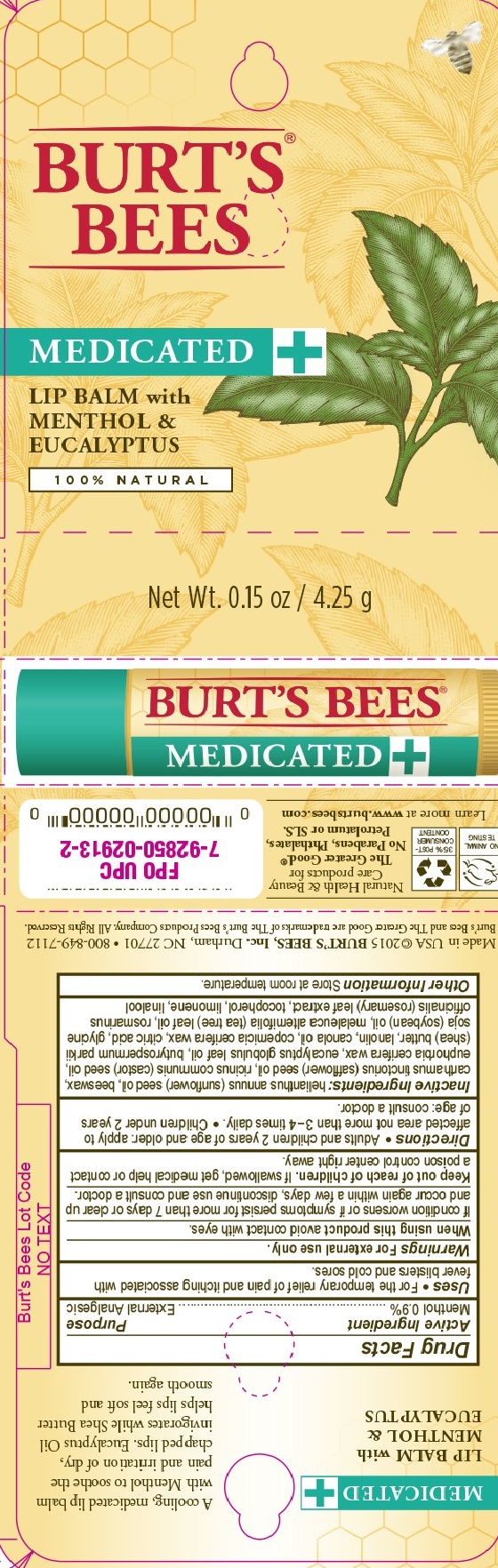 DRUG LABEL: MEDICATED LIP BALM
NDC: 26052-029 | Form: STICK
Manufacturer: Burt's Bees, Inc.
Category: otc | Type: HUMAN OTC DRUG LABEL
Date: 20181221

ACTIVE INGREDIENTS: MENTHOL 0.9 g/100 g
INACTIVE INGREDIENTS: ANHYDROUS CITRIC ACID; SUNFLOWER OIL; WHITE WAX; EUCALYPTUS OIL; SHEA BUTTER; LANOLIN; CASTOR OIL; CARNAUBA WAX; TEA TREE OIL; CANDELILLA WAX; SAFFLOWER OIL; CANOLA OIL; SOYBEAN OIL; ROSMARINUS OFFICINALIS FLOWERING TOP; TOCOPHEROL

Medicated Lip Balm (menth & euc)

ACTIVE INGREDIENT

MENTHOL 0.9%

PURPOSE

EXTERNAL ANALGESIC

USES

FOR THE TEMPORARY RELIEF OF PAIN AND ITCHING ASSOCIATED WITH FEVER BLISTERS AND COLD SORES

WARNINGS

FOR EXTERNAL USE ONLY.

IF CONDITION WORSENS OR IF SYMPTOMS PERSIST FOR MORE THAN 7 DAYS OR CLEAR UP AND OCCUR AGAIN WITHIN A FEW DAYS, DISCONTINUE USE AND CONSULT A DOCTOR.

WHEN USING THIS PRODUCT

AVOID CONTACT WITH EYES

KEEP OUT OF REACH OF CHUILDREN

IF SWALLOWED, GET MEDICAL HELP OR CONTACT A POISON CONTROL CENTER RIGHT AWAY.

DIRECTIONS

ADULTS AND CHILDREN 2 YEARS OF AGE AND OLDER: APPLY TO AFFECTED AREA NOT MORE THAN 3 TO 4 TIMES DAILY.

CHILDREN UNDER 2 YEARS OF AGE: CONSULT A DOCTOR.

INACTIVE INGREDIENTS

HELIANTHUS ANNUUS (SUNFLOWER) SEED OIL, BEESWAX, CARTHAMUS TINCTORIUS (SAFFLOWER) SEED OIL, RICINUS COMMUNIS (CASTOR) SEED OIL, EUPHORBIA CERIFERA WAX, EUCALYPTUS GLOBULUS LEAF OIL, BUTYROSPERMUM PARKII (SHEA) BUTTER, LANOLIN, CANOLA OIL, COPERNICA CERIFERA WAX, CITRIC ACID, GLYCINE SOJA (SOYBEAN) OIL, MELALEUCA ALTEMIFOLIA (TEA TREE) LEAF OIL, ROSMARINUS OFFICINALIS (ROSEMARY) LEAF EXTRACT, TOCOPHEROL, LIMONENE, LINALOOL.

OTHER INFORMATION

STORE AT ROOM TEMPERATURE

PDP

BURTS BEES

MEDICATED

LIP BALM WITH MENTHOL AND EUCALYPTUS